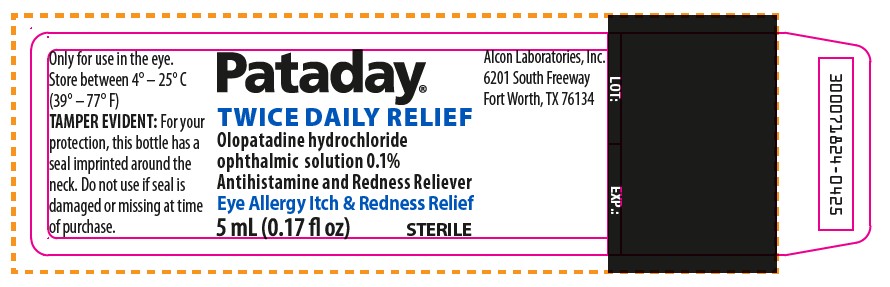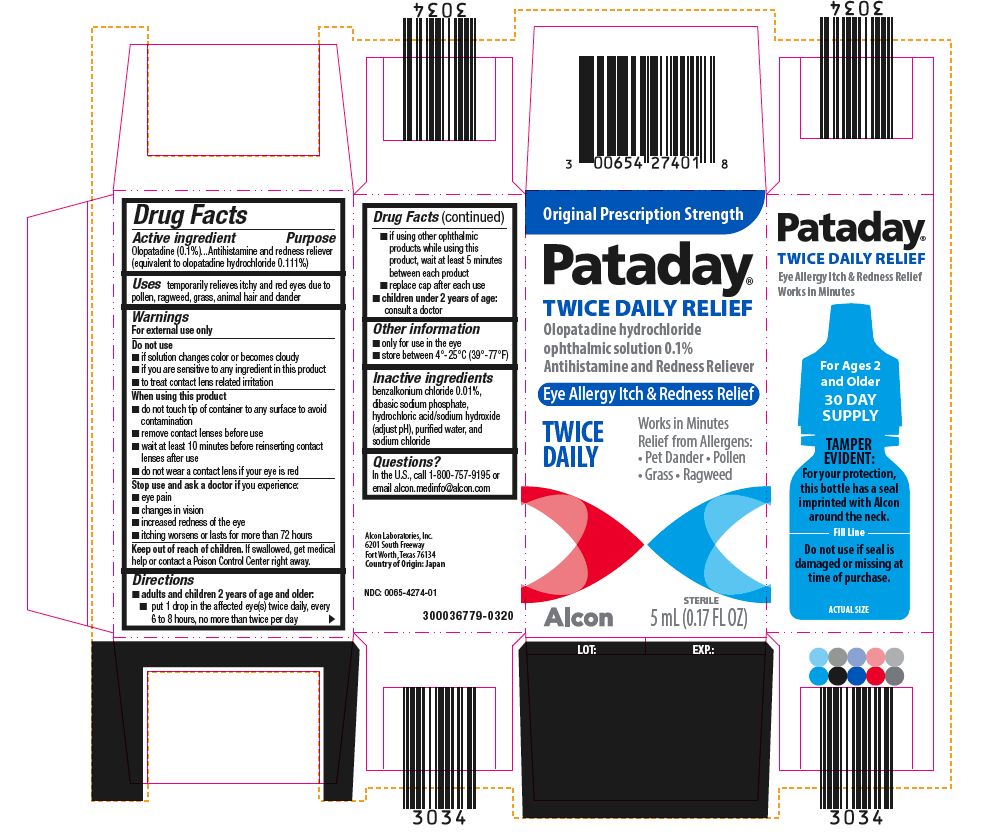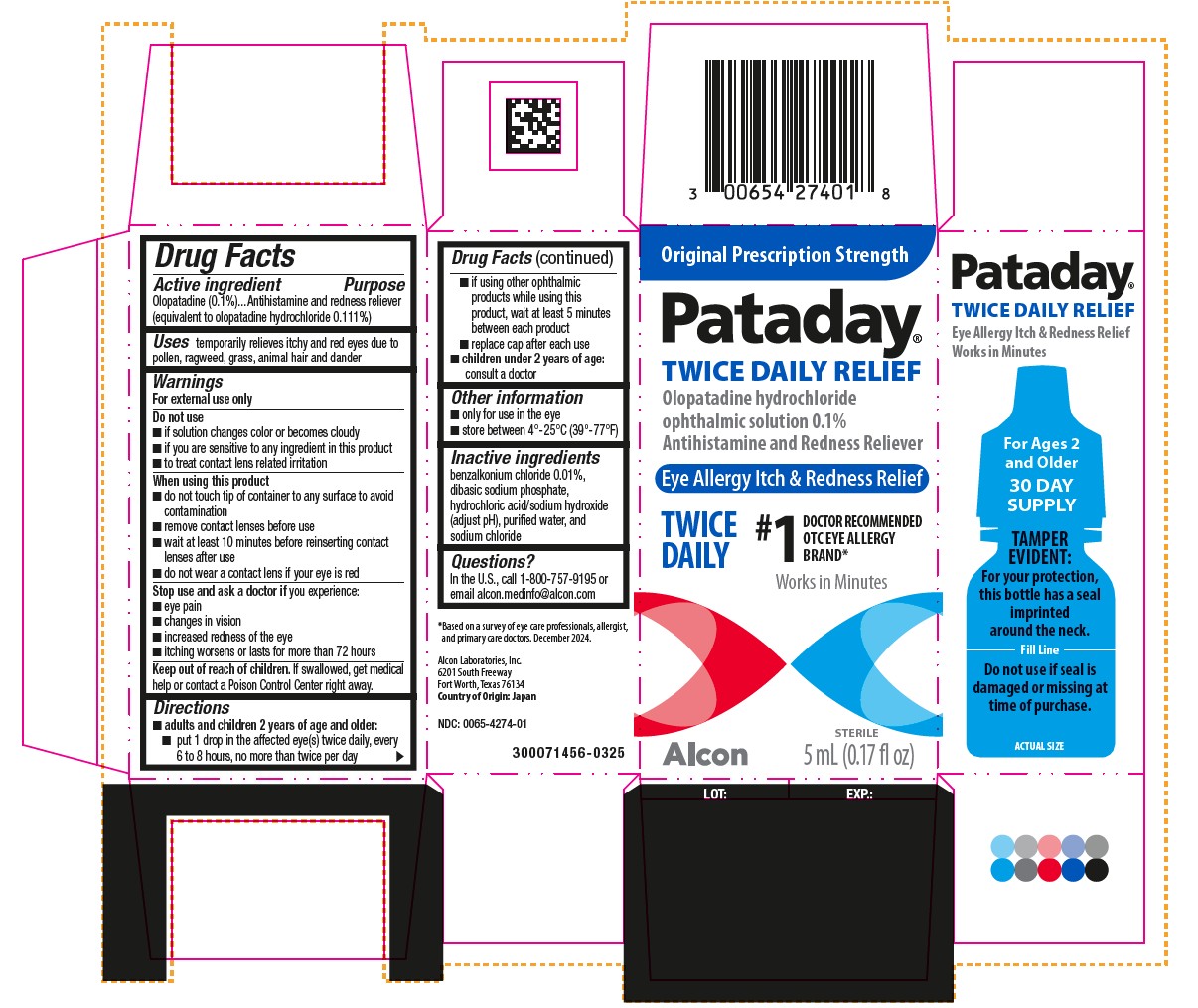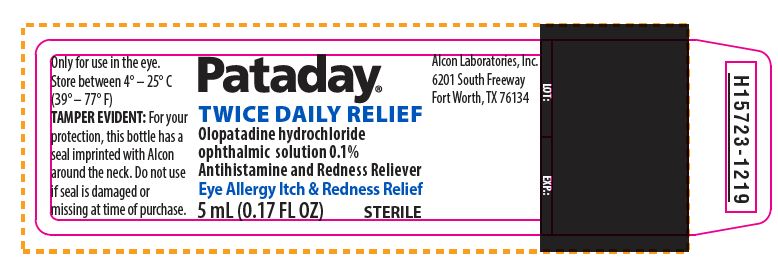 DRUG LABEL: PATADAY TWICE A DAY RELIEF
NDC: 0065-4274 | Form: SOLUTION
Manufacturer: Alcon Laboratories, Inc.
Category: otc | Type: HUMAN OTC DRUG LABEL
Date: 20260120

ACTIVE INGREDIENTS: Olopatadine Hydrochloride 1 mg/1 mL
INACTIVE INGREDIENTS: Sodium Phosphate, Dibasic, Unspecified Form; Sodium Chloride; Benzalkonium Chloride; Hydrochloric Acid; Sodium Hydroxide; Water

Drug Facts

ACTIVE INGREDIENT

Active Ingredients | Purpose
Olopatadine (0.1%). (equivalent to olopatadine hydrochloride 0.111%) | Antihistamine and Redness Reliever

INDICATIONS AND USAGE

Use temporarily relieves itchy and red eyes due to pollen, ragweed, grass, animal hair and dander

Warnings
For external use only

Do not use

- if solution changes color or becomes cloudy
- if you are sensitive to any ingredient in this product
- to treat contact lens related irritation

When using this product

- do not touch tip of container to any surface to avoid contamination
- remove contact lenses before use
- wait at least 10 minutes before reinserting contact lenses after use
- do not wear a contact lens if your eye is red

Stop use and ask a doctor if you experience:

- eye pain
- changes in vision
- increased redness of the eye
- itching worsens or lasts for more than 72 hours

Keep out of reach of children. If swallowed, get medical help or contact a Poison Control Center right away.

Directions

- adults and children 2 years of age and older:
  - put 1 drop in the affected eye(s) twice daily, every 6 to 8 hours, no more than twice per day
  - if using other ophthalmic products while using this product, wait at least 5 minutes between each product
  - replace cap after each use
- children under 2 years of age: consult a doctor

Other information

- only for use in the eye
- store between 4°-25°C (39°-77°F)

Inactive ingredients

benzalkonium chloride 0.01%, dibasic sodium phosphate, hydrochloric acid/sodium hydroxide (adjust pH), purified water, and sodium chloride

Questions?

In the U.S., call 1-800-757-9195 or email alcon.medinfo@alcon.com

Alcon Laboratories, Inc.
6201 South Freeway
Fort Worth, Texas 76134
Country of Origin: Japan

NDC: 0065-4274-01
9017919-1219

PRINCIPAL DISPLAY PANEL

Original Prescription Strength
Pataday®
TWICE DAILY RELIEF
Olopatadine hydrochloride
ophthalmic solution 0.1%
Antihistamine and Redness Reliever
Eye Allergy Itch & Redness Relief
TWICE DAILY
Works in Minutes
Relief from Allergens:
• Pet Dander
• Pollen
• Grass
• Ragweed
STERILE
5 mL (0.17 FL OZ)
Alcon
Pataday®
TWICE DAILY RELIEF
Eye Allergy Itch & Redness Relief
Works in Minutes
For Ages 2 and Older
30 DAY SUPPLY
TAMPER EVIDENT: For your protection, this bottle has a seal imprinted with Alcon around the neck.
________Fill Line________
Do not use if seal is damaged or missing at time of purchase.
ACTUAL SIZE
Alcon Laboratories, Inc.
6201 South Freeway
Fort Worth, Texas 76134
Country of Origin: Japan
NDC: 0065-4274-01
300036779-0320
LOT: EXP.:

Pataday®
TWICE DAILY RELIEF
Olopatadine hydrochloride
ophthalmic solution 0.1%
Antihistamine and Redness Reliever
Eye Allergy Itch & Redness Relief
5 mL (0.17 FL OZ)
STERILE
Only for use in the eye.
Store between 4° – 25° C (39° – 77° F)
TAMPER EVIDENT: For your protection, this bottle has a seal imprinted with Alcon around the neck. Do not use if seal is damaged or missing at time of purchase.
Alcon Laboratories, Inc.
6201 South Freeway
Fort Worth, TX 76134
LOT: EXP.:
H15723-1219

Original Prescription Strength
Pataday®
TWICE DAILY RELIEF
Olopatadine hydrochloride
ophthalmic solution 0.1%
Antihistamine and Redness Reliever
Eye Allergy Itch & Redness Relief
TWICE
DAILY
#1 DOCTOR RECOMMENDED
OTC EYE ALLERGY
BRAND*
Works in Minutes
STERILE
5 mL (0.17 fl oz)
Alcon
LOT: EXP.:
Pataday®
TWICE DAILY RELIEF
Eye Allergy Itch & Redness Relief
Works in Minutes
For Ages 2
and Older
30 DAY
SUPPLY
TAMPER EVIDENT:
For your protection,
this bottle has a seal
imprinted
around the neck.
________Fill Line________
Do not use if seal is
damaged or missing at
time of purchase.
ACTUAL SIZE
*Based on a survey of eye care professionals,
allergists, and primary care doctors. December 2024.
Alcon Laboratories, Inc.
6201 South Freeway
Fort Worth, Texas 76134
Country of Origin: Japan
NDC: 0065-4274-01
300071456-0325

Pataday®
TWICE DAILY RELIEF
Olopatadine hydrochloride
ophthalmic solution 0.1%
Antihistamine and Redness Reliever
Eye Allergy Itch & Redness Relief
5 mL (0.17 fl oz) STERILE
Only for use in the eye.
Store between 4° – 25° C
(39° – 77° F)
TAMPER EVIDENT: For your
protection, this bottle has a
seal imprinted around the
neck. Do not use if seal is
damaged or missing at time
of purchase.
Alcon Laboratories, Inc.
6201 South Freeway
Fort Worth, TX 76134
LOT: EXP.:
300071824-0425